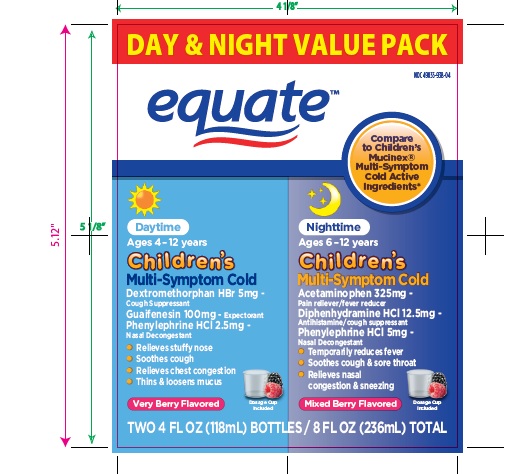 DRUG LABEL: Daytime Nighttime Childrens Multi-symptom Cold
NDC: 49035-938 | Form: KIT | Route: ORAL
Manufacturer: Wal-Mart Stores, Inc.
Category: otc | Type: Human OTC Drug Label
Date: 20241126

ACTIVE INGREDIENTS: DEXTROMETHORPHAN HYDROBROMIDE 5 mg/5 mL; GUAIFENESIN 100 mg/5 mL; PHENYLEPHRINE HYDROCHLORIDE 2.5 mg/5 mL; ACETAMINOPHEN 325 mg/10 mL; DIPHENHYDRAMINE HYDROCHLORIDE 12.5 mg/10 mL; PHENYLEPHRINE HYDROCHLORIDE 5 mg/10 mL
INACTIVE INGREDIENTS: ANHYDROUS CITRIC ACID; D&C RED NO. 33; DEXTROSE, UNSPECIFIED FORM; EDETATE DISODIUM; FD&C BLUE NO. 1; FD&C RED NO. 40; GLYCERIN; METHYLPARABEN; POTASSIUM SORBATE; PROPYL GALLATE; PROPYLENE GLYCOL; PROPYLPARABEN; WATER; SACCHARIN SODIUM; SODIUM HYDROXIDE; SORBITOL; SUCRALOSE; XANTHAN GUM; ANHYDROUS CITRIC ACID; EDETATE DISODIUM; FD&C BLUE NO. 1; FD&C RED NO. 40; GLYCERIN; PROPYLENE GLYCOL; PROPYL GALLATE; WATER; SODIUM BENZOATE; SODIUM CITRATE; SORBITOL; SUCRALOSE; XANTHAN GUM

Daytime Nighttime Children's Multi-Symptom Cold

ACTIVE INGREDIENT(S) FOR DAYTIME (in each 5 mL)

Dextromethorphan HBr 5mg

Guaifenesin 100 mg

Phenylephrine HCl 2.5 mg

ACTIVE INGREDIENT(S) FOR NIGHTTIME (in each 10 mL)

Acetaminophen 325 mg
Diphenhydramine HCl 12.5 mg
Phenylephrine HCl 5 mg

PURPOSE FOR DAYTIME

Cough Suppressant

Expectorant

Nasal decongestant

PURPOSE FOR NIGHTTIME

Pain reliever/fever reducer
Antihistamine/Cough Suppressant
Nasal decongestant

USE(S)

DAYTIME

- helps loosen phlegm (mucus) and thin bronchial secretions to drain bronchial tubes and make coughs more productive
- temporarily relieves:
- cough due to minor throat and bronchial irritation as may occur with a cold or inhaled irritants
- the intensity of coughing
- the impulse to cough to help your child get to sleep
- nasal congestion due to a cold
- stuffy nose

NIGHTTIME

- temporarily relieves these common cold and flu symptoms:

- cough
- sore throat
- nasal congestion
- runny nose
- minor aches and pains
- headache
- sinus congestion and pressure
- sneezing

- temporarily reduces fever
- controls cough to help your child get to sleep

WARNINGS

NIGHTTIME

Liver warning: This product contains acetaminophen. Severe liver damage may occur if your child takes

- more than 5 doses in 24 hours, which is the maximum daily amount
- with other drugs containing acetaminophen

Allergy alert: acetaminophen may cause severe skin reactions. Symptoms may include:

- skin reddening
- blisters
- rash

If a skin reaction occurs, stop use and seek medical help right away.
Sore throat warning: if sore throat is severe, persists for more than 2 days, is accompanied or followed by fever, headache, rash, nausea or vomiting, consult a doctor promptly.

DO NOT USE

DAYTIME
in a child who is taking a prescription monoamine oxidase inhibitor (MAOI) (certain drugs for depression, psychiatric, or emotional conditions, or Parkinson's disease), or for 2 weeks after stopping the MAOI drug. If you do not know if your child's prescription drug contains an MAOI, ask a doctor or pharmacist before giving this product.
NIGHTTIME

- with any other drug containing acetaminophen (prescription or nonprescription). If you are not sure whether a drug contains acetaminophen, ask a doctor or pharmacist.
- to make a child sleepy
- with any other product containing diphenhydramine, even one used on the skin
- in a child who is taking a prescription monoamine oxidase inhibitor (MAOI) (certain drugs for depression, psychiatric, or emotional conditions, or Parkinson's disease), or for 2 weeks after stopping MAOI drug. If you do not know if your child prescription drug contains an MAOI, ask a doctor or pharmacist before giving this product.

ASK A DOCTOR BEFORE USE IF CHILD HAS

DAYTIME

- heart disease
- high blood pressure
- thyroid disease
- diabetes
- persistent or chronic cough such as occurs with asthma
- cough that occurs with too much phlegm (mucus)

NIGHTTIME

- liver disease
- thyroid disease
- diabetes
- heart disease
- high blood pressure
- glaucoma
- a breathing problem such as chronic bronchitis
- persistent or chronic cough such as occurs with asthma
- cough that occurs with too much phlegm (mucus)

ASK A DOCTOR OR PHARMACIST BEFORE USE IF YOUR CHILD

NIGHTTIME

- is taking the blood thinning drug warfarin
- taking sedatives or tranquilizers

WHEN USING THIS PRODUCT

DAYTIME

do not use more than directed

NIGHTTIME

- do not use more than directed (see Overdose warning)
- excitability may occur, especially in children
- marked drowsiness may occur
- sedatives and tranquilizers may increase drowsiness

STOP USE AND ASK DOCTOR IF

DAYTIME

- your child gets nervous, dizzy or sleepless
- symptoms do not get better within 7 days or occur with fever
- cough lasts more than 7 days, comes back, or occurs with fever, rash, or persistent headache.

These could be signs of a serious illness.
NIGHTTIME

- nervousness, dizziness or sleeplessness occur
- pain, nasal congestion or cough gets worse or lasts more than 5 days
- fever gets worse or lasts more than 3 days
- redness or swelling is present
- new symptoms occur
- cough comes back, or occurs with fever, rash or headache that lasts. These could be signs of a serious condition.

KEEP OUT OF REACH OF CHILDREN

DAYTIME

In case of overdose, get medical help or contact a Poison Control Center right away.
NIGHTTIME
Overdose warning: Taking more than the recommended dose (overdose) may cause liver damage. In case of overdose, get medical help or contact a Poison Control Center right away. Quick medical attention is critical even if you do not notice any signs or symptoms.

DIRECTIONS

DAYTIME

- do not take more than 6 doses in any 24-hour period
- measure only with dosing cup provided
- do not use dosing cup with other products
- dose as follows or as directed by a doctor

Age | Dose
children 6 years to under 12 years | 10 mL every 4 hours
children 4 years to under 6 years | 5 mL every 4 hours
children under 4 years | do not use

- mL = milliliter

NIGHTTIME

- this product does not contain directions or complete warnings for adult use
- do not give more than directed (see Overdose warning)
- shake well before use
- do not give more than 5 doses in any 24-hour period
- if needed, repeat dose every 4 hours while symptoms last
- do not give more than 5 days unless directed by a doctor
- measure only with dosing cup provided
- do not use dosing cup with other products
- dose as follows or as directed by a doctor
- mL = milliliter
- children 6 to under 12 years of age: 10 mL in dosing cup provided.
- children under 6 years of age: do not use.

OTHER INFORMATION

DAYTIME

- each 5 mL contains: potassium 5 mg, sodium 5 mg
- store between 15-30°C (59-86°F)
- do not refrigerate
- dosing cup provided

NIGHTTIME

- each 10 mL contains: sodium 10 mg
- store between 15-30°C (59-86°F)
- do not refrigerate
- dosing cup provided

INACTIVE INGREDIENTS

DAYTIME

citric acid anhydrous, D&C red # 33, dextrose, edetate disodium, FD&C blue # 1, FD&C Red #40, flavor, glycerin, methylparaben, potassium sorbate, propyl gallate, propylene glycol, propylparaben, purified water, saccharin sodium, sodium hydroxide, sorbitol solution, sucralose, xanthan gum.
NIGHTTIME
citric acid anhydrous, edetate disodium, FD&C blue # 1, FD&C Red #40, flavors, glycerin, propylene glycol, propyl gallate, purified water, sodium benzoate, sodium citrate, sorbitol, sucralose, xanthan gum.

QUESTIONS OR COMMENTS?

call 1-888-287-1915

PRINCIPAL DISPLAY PANEL

DAY & NIGHT VALUE PACK

NDC 49035-938-04

equateTM

Compare to Children's Mucinex®Multi-Symptom Cold Active Ingredients*

Daytime

Ages 4-12 years

Children's Multi-Symptom Cold
Dextromethorphan HBr 5mg - Cough Suppressant

Guaifenesin 100mg - Expectorant

Phenylephrine HCl 2.5 mg - Nasal Decongestant

- Relieves Stuffy Nose

- Soothes Cough
- Relieves Chest Congestion
- Thins & loosens Mucus

Very Berry Flavored

Dosage cup included

NIGHTTIME

Ages 6-12 years Children's Multi-Symptom Cold Acetaminophen 325mg - Pain reliever/fever reducer Diphenhydramine HCl 12.5mg - Antihistamine/cough suppressant
Phenylephrine HCl 5 mg - Nasal Decongestant

- Temporarily reduces fever
- Soothes cough & sore throat
- Relieves nasal congestion & sneezing

Mixed berry flavored Dosage Cup Included
TWO 4 FL OZ (118 mL) BOTTLES / 8 FL OZ (236 mL) TOTAL